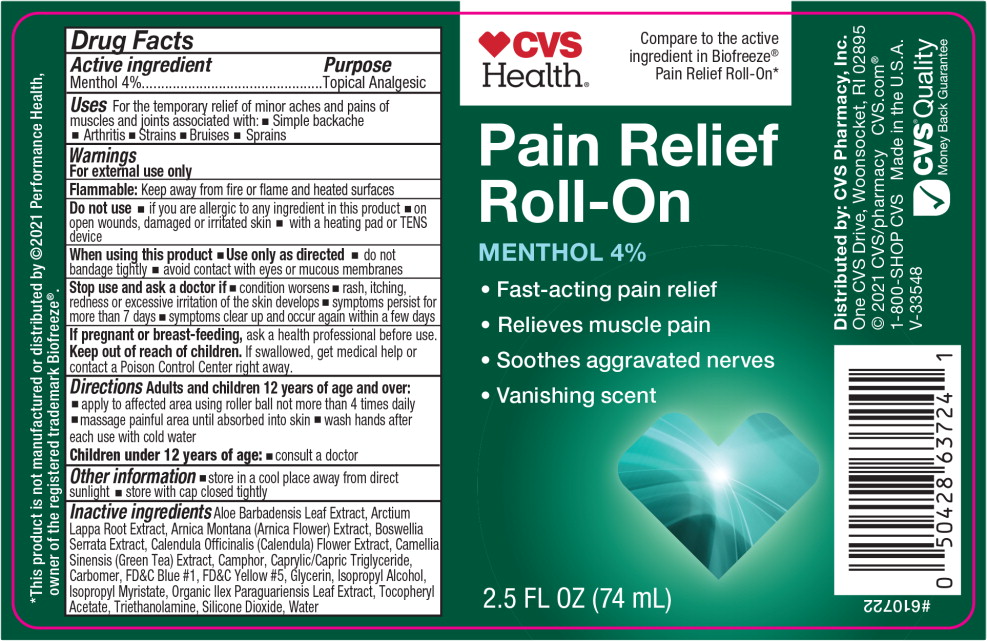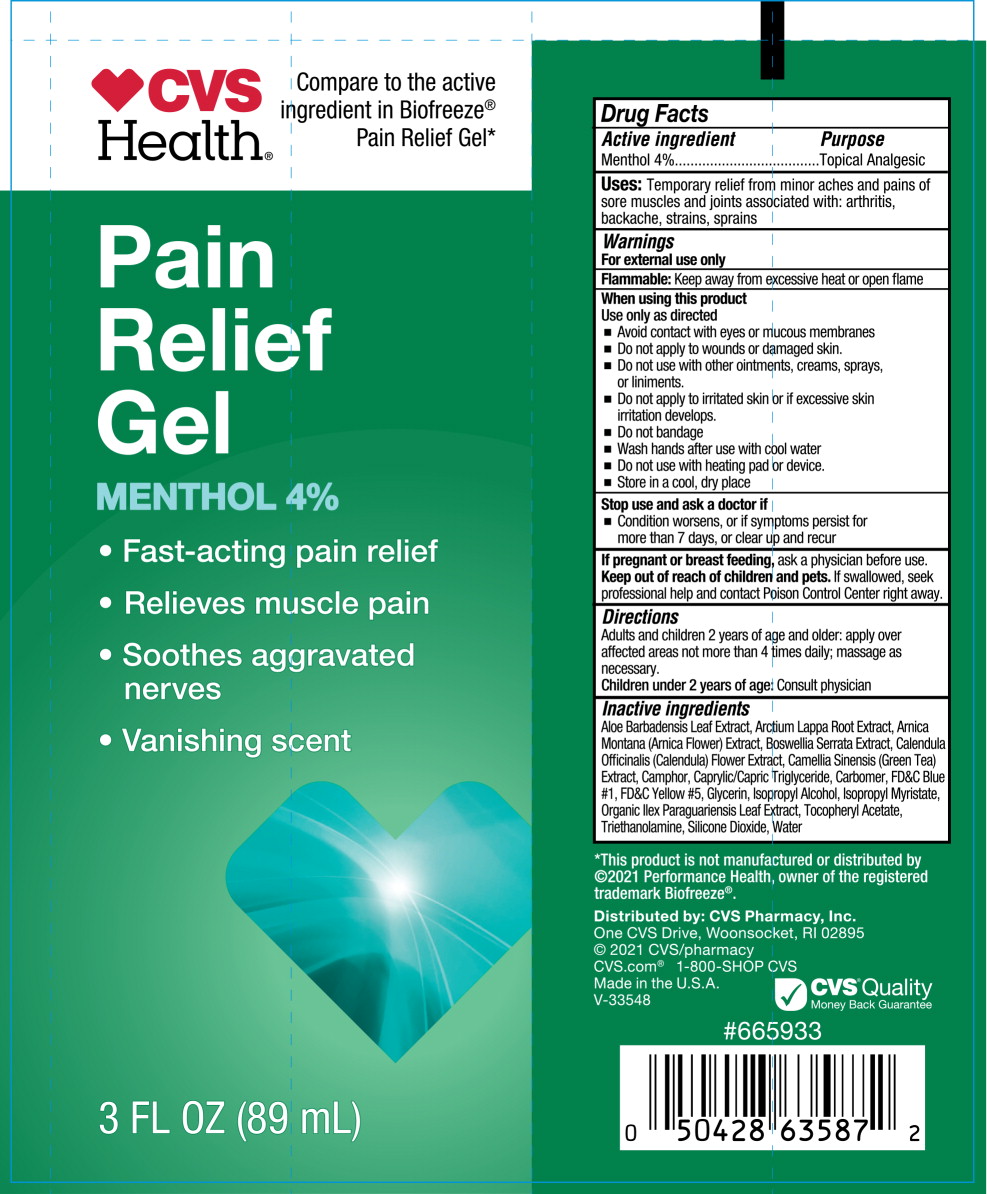 DRUG LABEL: CVS Pain Relief
NDC: 51316-933 | Form: GEL
Manufacturer: CVS Pharmacy
Category: otc | Type: HUMAN OTC DRUG LABEL
Date: 20260212

ACTIVE INGREDIENTS: MENTHOL, UNSPECIFIED FORM 40 mg/1 mL
INACTIVE INGREDIENTS: FD&C BLUE NO. 1; FRANKINCENSE; CAPRYLIC/CAPRIC TRIGLYCERIDE; CALENDULA OFFICINALIS FLOWER; FD&C YELLOW NO. 5; ILEX PARAGUARIENSIS LEAF; .ALPHA.-TOCOPHEROL ACETATE; ALOE BARBADENSIS LEAF JUICE; ISOPROPYL ALCOHOL; GLYCERIN; CAMELLIA SINENSIS LEAF; CAMPHOR (SYNTHETIC); CARBOMER 940; WATER; SILICON DIOXIDE; TROLAMINE; ISOPROPYL MYRISTATE; ARCTIUM LAPPA ROOT; ARNICA MONTANA FLOWER

CVS Pain Relief

Active ingredient

Menthol 4%

Purpose

Topical Analgesic

Uses

For the temporary relief of minor aches and pains of muscles and joints associated with:

- simple backache
- arthritis
- strains
- bruises
- sprains

Warnings

For external use only

Flammable: Keep away from fire or flame and heated surfaces

Do not use

- if you are allergic to any ingredient in this product
- on open wounds, damaged or irritated skin
- with a heating pad or TENS device

When using this product

Use only as directed

- Avoid contact with eyes or mucous membranes
- Do not apply to wounds or damaged skin.
- Do not use wiht other ointments, creams, sprays, or liniments
- Do not apply to irritated skin or if excessive skin irritation develops
- Do not bandage
- Wash hands after use with cool water
- Do not use with heating pad or device
- Store in a cool, dry place

Stop use and ask a doctor if

- condition worsens, or if symptoms persist for more than 7 days, or clear up and recur

If pregnant or breast feeding,

ask a physician before use.

Keep out of reach of children and pets.

If swallowed, seek professional help and contact Poison Control Center right away.

Directions

Adults and children 2 years of age and older: apply over affected areas not more than 4 times daily; massage as necessary.

Children under 2 years of age: Consult a physician

Inactive ingredients

Aloe Barbadensis Leaf Extract, Arctium Lappa Root Extract, Arnica Montana (Arnica Flower) Extract, Boswellia Serrata Extract, Calendula Officinalis (Calendula) Flower Extract, Camellia Sinensis (Green Tea) Extract, Camphor, Caprylic/Capric Triglyceride, Carbomer, FD&C Blue #1, FD&C Yellow #5, Glycerin, Isopropyl Alcohol, Isopropyl Myristate, Organic Ilex Paraguariensis Leaf Extract, Tocopheryl Acetate, Triethanolamine, Silicone Dioxide, Water

Principal Display Panel - 74 mL Bottle Label

CVS Health®

Compare to the active ingredient in Biofreeze® Pain Relief Roll-On*

Pain Relief Roll-On

MENTHOL 4%

- Fast-acting pain relief
- Relieves muscle pain
- Soothes aggravated nerves
- Vanishing scent

2.5 FL OZ (74 mL)

Principal Display Panel - 89 mL Tube Label

CVS Health®

Compare to the active ingredient in Biofreeze® Pain Relief Gel*

Pain Relief Gel

MENTHOL 4%

- Fast-acting pain relief
- Relieves muscle pain
- Soothes aggravated nerves
- Vanishing scent

3 FL OZ (89 mL)